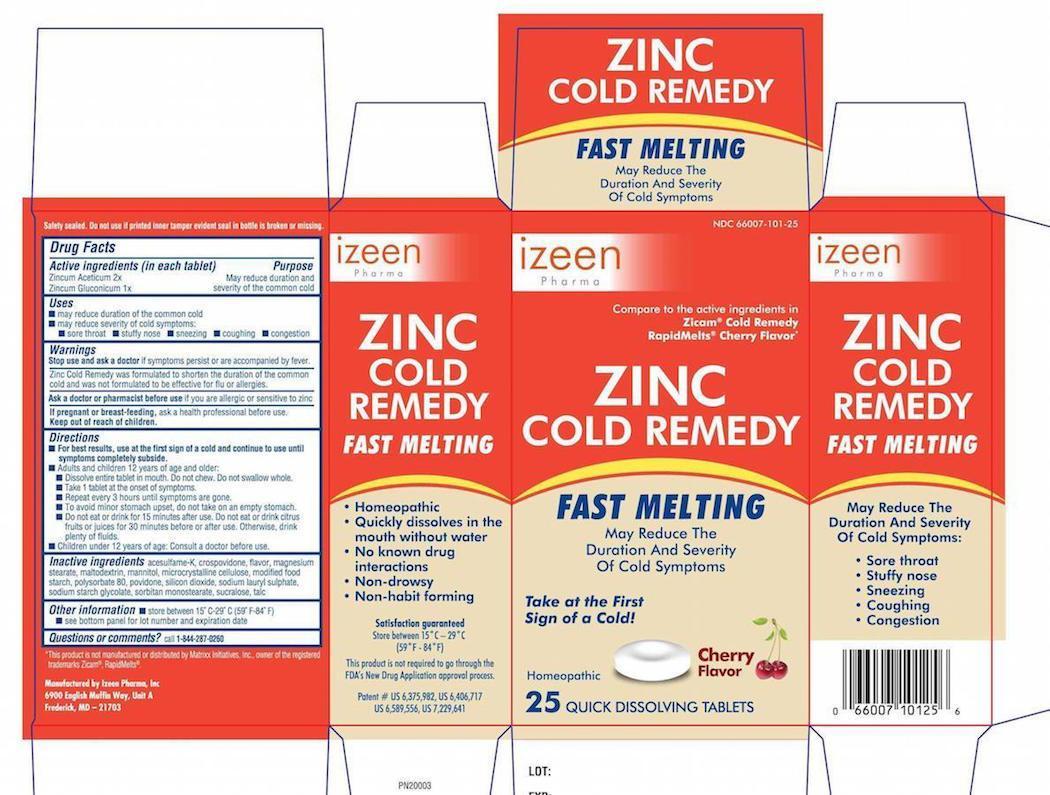 DRUG LABEL: Zinc Cold Remedy Fast Melting
NDC: 66007-101 | Form: TABLET
Manufacturer: Izeen Pharma, Inc.
Category: homeopathic | Type: HUMAN OTC DRUG LABEL
Date: 20150209

ACTIVE INGREDIENTS: ZINC ACETATE 2 [hp_X]/1 1; ZINC GLUCONATE 1 [hp_X]/1 1
INACTIVE INGREDIENTS: SODIUM STARCH GLYCOLATE TYPE A POTATO; POLYSORBATE 80; SODIUM LAURYL SULFATE; MAGNESIUM STEARATE; MANNITOL; SORBITAN; MODIFIED CORN STARCH (1-OCTENYL SUCCINIC ANHYDRIDE); CELLULOSE, MICROCRYSTALLINE; STEARIC ACID; SUCRALOSE; TALC; ACESULFAME POTASSIUM

Zinc Cold Remedy Fast Melting -Cherry Flavor

Drug Facts

Active ingredients (in each tablet)

Zincum aceticum 2x
Zincum gluconicum 1x

Purpose

Reduces duration and severity of the common cold

Uses

- may reduce duration of the common cold
- may reduce the severity of cold symptoms
  - stuffy nose
  - sneezing
  - coughing
  - nasal congestion

Warnings

Ask a doctor before use if you have

Warnings

Zinc Cold Remedy was formulated to shorten the duration of the common cold and is not forulated to be effective for the flu or allergies.

Ask your doctor or pharmacist if you are allergic or sensitive to zinc.

Stop use and ask a doctor if symptoms persist or are accompanied by fever

PREGNANCY OR BREAST FEEDING

If pregnant or breast-feeding, ask a health professional before use.

Keep out of reach of children. In case of overdose, get medical help or contact a Poison Control Center right away.

Directions

- for best results, use at the first sign of a cold and continue to use until symptoms completely subside
- adults and children 12 years of age and older:
  - take 1 tablet at the onset of symptoms
  - dissolve entire tablet in mouth. Do not chew. Do not swallow whole.
  - repeat every 4-6 hours, not to exceed 4 tablets in 24 hours
  - to avoid minor stomach upset, do not take on an empty stomach
  - do not eat or drink for 15 minutes after use. Do not eat or drink citrus fruits or juices for 30 minutes before or after use. Otherwise, drink plenty of fluids.
- children under 12 years of age: ask a doctor before use

Other information

- store between 15-29° (59-84°F)

Inactive ingredients

acesulfame –K, crospovidone, magnisium streate, mannatol, microcrystalline celulose , polysorbate 80, modified food starch , soodium lauryl sulfate, sodium starch glycolate, sorbitan monostearate, sucralose, talc.

Questions/Comments

Questions/Comments call 1-844-287-0260

Manufactured by Izeen Pharma, Inc. 6900 English Muffin Way, Unit A, Frederick, MD 21703